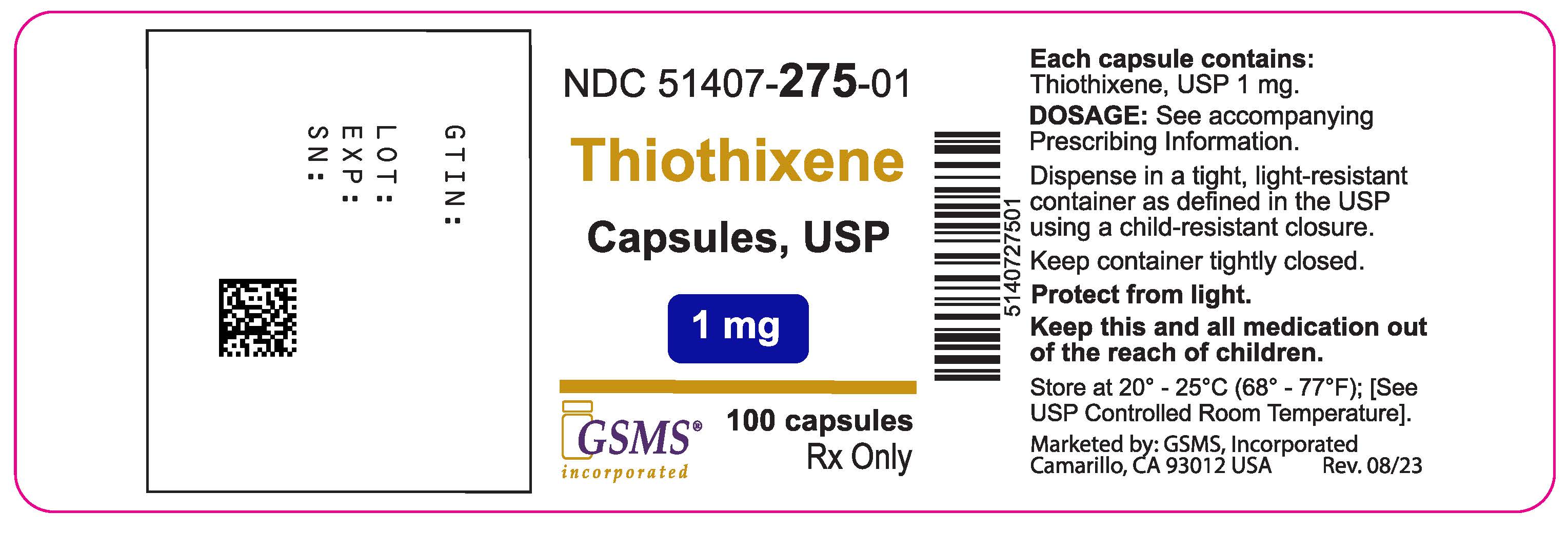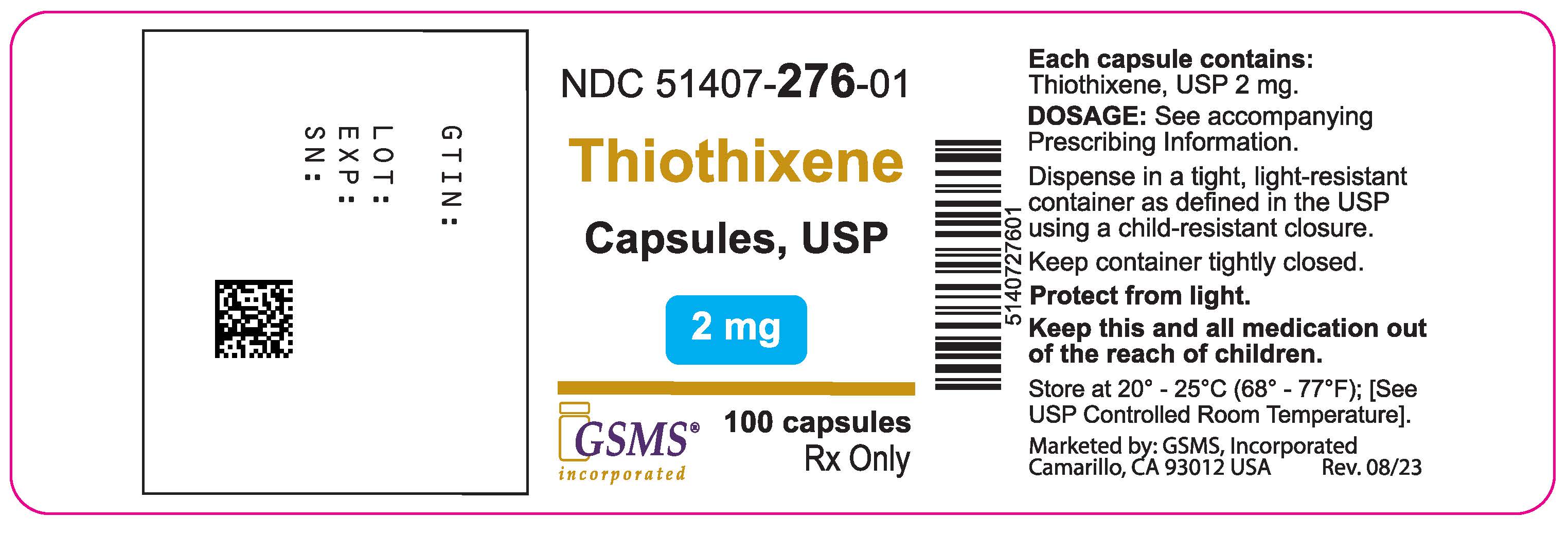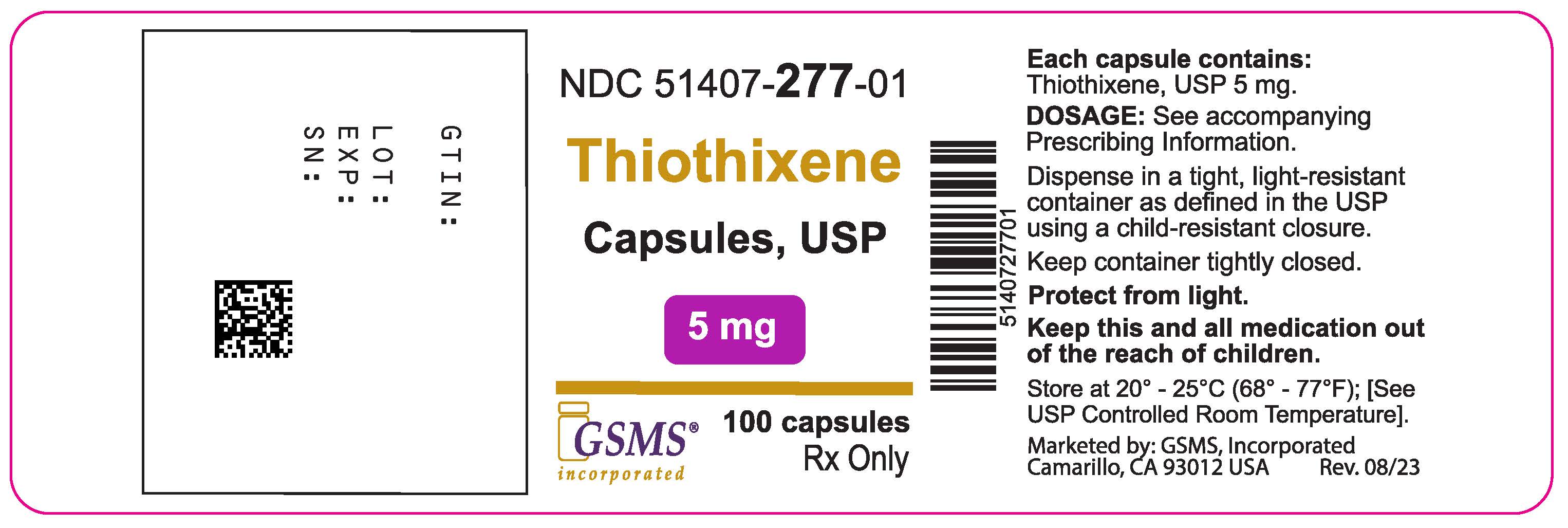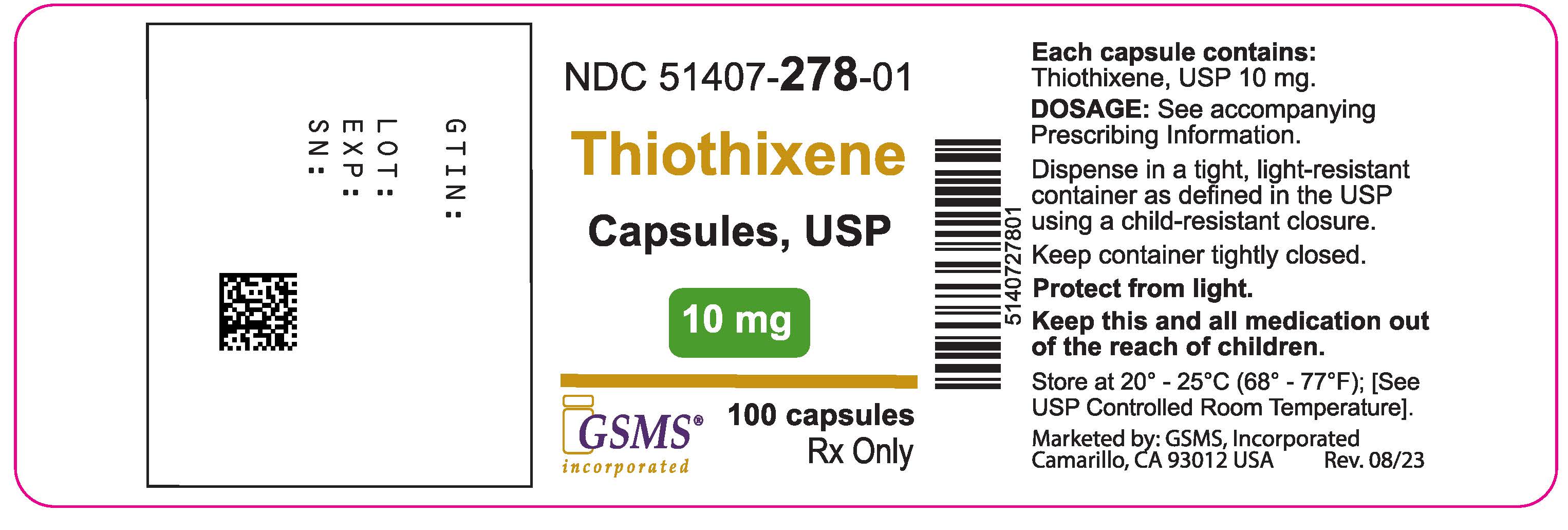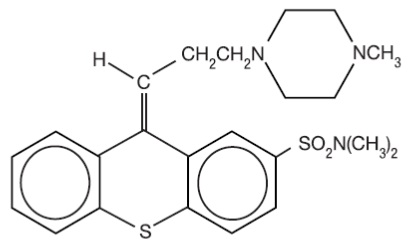 DRUG LABEL: Thiothixene
NDC: 51407-275 | Form: CAPSULE
Manufacturer: Golden State Medical Supply, Inc.
Category: prescription | Type: HUMAN PRESCRIPTION DRUG LABEL
Date: 20250411

ACTIVE INGREDIENTS: THIOTHIXENE 1 mg/1 1
INACTIVE INGREDIENTS: LACTOSE MONOHYDRATE; CELLULOSE, MICROCRYSTALLINE; CROSCARMELLOSE SODIUM; STARCH, CORN; SILICON DIOXIDE; MAGNESIUM STEARATE; SODIUM LAURYL SULFATE; FD&C BLUE NO. 1; FD&C RED NO. 40; FD&C YELLOW NO. 6; TITANIUM DIOXIDE; GELATIN; SHELLAC; PROPYLENE GLYCOL; AMMONIA; POTASSIUM HYDROXIDE; FERROSOFERRIC OXIDE; D&C RED NO. 28

Thiothixene Capsules, USP
Rx Only

BOXED WARNING

WARNING
Increased Mortality in Elderly Patients with Dementia-Related Psychosis: Elderly patients with dementia-related psychosis treated with antipsychotic drugs are at an increased risk of death. Analyses of seventeen placebo-controlled trials (modal duration of 10 weeks), largely in patients taking atypical antipsychotic drugs, revealed a risk of death in drug-treated patients of between 1.6 to 1.7 times the risk of death in placebo-treated patients. Over the course of a typical 10-week controlled trial, the rate of death in drug-treated patients was about 4.5%, compared to a rate of about 2.6% in the placebo group. Although the causes of death were varied, most of the deaths appeared to be either cardiovascular (e.g., heart failure, sudden death) or infectious (e.g., pneumonia) in nature. Observational studies suggest that, similar to atypical antipsychotic drugs, treatment with conventional antipsychotic drugs may increase mortality. The extent to which the findings of increased mortality in observational studies may be attributed to the antipsychotic drug as opposed to some characteristic(s) of the patients is not clear. Thiothixene is not approved for the treatment of patients with dementia-related psychosis (see WARNINGS).

DESCRIPTION

Thiothixene is a thioxanthene derivative. Specifically, it is the cis isomer of N,N-dimethyl-9-[3-(4- methyl-1-piperazinyl)propylidene]thioxanthene-2-sulfonamide. It may be represented by the following structural formula

The thioxanthenes differ from the phenothiazines by the replacement of nitrogen in the central ring with a carbon-linked side chain fixed in space in a rigid structural configuration. An N,N-dimethyl sulfonamide functional group is bonded to the thioxanthene nucleus.
Each capsule contains 1 mg, 2 mg, 5 mg or 10 mg of thiothixene, USP and the following inactive ingredients: colloidal silicon dioxide, croscarmellose sodium, lactose monohydrate, magnesium stearate, microcrystalline cellulose, pregelatinized starch and sodium lauryl sulfate. Each of the empty gelatin capsules contains FD&C Blue No. 1, FD&C Red No. 40, FD&C Yellow No. 6, gelatin, sodium lauryl sulfate and titanium dioxide. In addition, the 1 mg empty gelatin capsules contain D&C Red No. 28 and the 2 mg empty gelatin capsules contain D&C Yellow No. 10.
The imprinting ink contains the following: ammonia solution, black iron oxide, potassium hydroxide, propylene glycol and shellac.

ACTION

Thiothixene is an antipsychotic of the thioxanthene series. Thiothixene possesses certain chemical and pharmacological similarities to the piperazine phenothiazines and differences from the aliphatic group of phenothiazines.

INDICATIONS & USAGE

Thiothixene capsules are effective in the management of schizophrenia. Thiothixene capsules have not been evaluated in the management of behavioral complications in patients with mental retardation.

CONTRAINDICATIONS

Thiothixene capsules are contraindicated in patients with circulatory collapse, comatose states, central nervous system depression due to any cause, and blood dyscrasias. Thiothixene is contraindicated in individuals who have shown hypersensitivity to the drug. It is not known whether there is a cross sensitivity between the thioxanthenes and the phenothiazine derivatives, but this possibility should be considered.

WARNINGS

Increased Mortality in Elderly Patients with Dementia-Related Psychosis
Elderly patients with dementia-related psychosis treated with antipsychotic drugs are at an increased risk of death. Thiothixene is not approved for the treatment of patients with dementia-related psychosis (see BOXED WARNING).
Tardive Dyskinesia
Tardive dyskinesia, a syndrome consisting of potentially irreversible, involuntary, dyskinetic movements may develop in patients treated with antipsychotic drugs, including thiothixene (1). Although the prevalence of the syndrome appears to be highest among the elderly, especially elderly women, it is impossible to rely upon prevalence estimates to predict, at the inception of antipsychotic treatment, which patients are likely to develop the syndrome. Whether antipsychotic drug products differ in their potential to cause tardive dyskinesia is unknown.
Both the risk of developing the syndrome and the likelihood that it will become irreversible are believed to increase as the duration of treatment and the total cumulative dose of antipsychotic drugs administered to the patient increase. However, the syndrome can develop, although much less commonly, after relatively brief treatment periods at low doses.
There is no known treatment for established cases of tardive dyskinesia, although the syndrome may remit, partially or completely, if antipsychotic treatment is withdrawn. Antipsychotic treatment, itself, however, may suppress (or partially suppress) the signs and symptoms of the syndrome and thereby may possibly mask the underlying disease process. The effect that symptomatic suppression has upon the long-term course of the syndrome is unknown.
Given these considerations, antipsychotics should be prescribed in a manner that is most likely to minimize the occurrence of tardive dyskinesia. Chronic antipsychotic treatment should generally be reserved for patients who suffer from a chronic illness that, 1) is known to respond to antipsychotic drugs, and 2) for whom alternative, equally effective, but potentially less harmful treatments are not available or appropriate. In patients who do require chronic treatment, the smallest dose and the shortest duration of treatment producing a satisfactory clinical response should be sought. The need for continued treatment should be reassessed periodically.
If signs and symptoms of tardive dyskinesia appear in a patient on antipsychotics, drug discontinuation should be considered. However, some patients may require treatment despite the presence of the syndrome.
(For further information about the description of tardive dyskinesia and its clinical detection, please refer to Information for Patients in the PRECAUTIONS section, and to the ADVERSE REACTIONS section.)
Neuroleptic Malignant Syndrome (NMS)
A potentially fatal symptom complex sometimes referred to as Neuroleptic Malignant Syndrome (NMS) has been reported in association with antipsychotic drugs, including thiothixene^2. Clinical manifestations of NMS are hyperpyrexia, muscle rigidity, altered mental status and evidence of autonomic instability (irregular pulse or blood pressure, tachycardia, diaphoresis, and cardiac dysrhythmias).
The diagnostic evaluation of patients with this syndrome is complicated. In arriving at a diagnosis, it is important to identify cases where the clinical presentation includes both serious medical illness (e.g., pneumonia, systemic infection, etc.) and untreated or inadequately treated extrapyramidal signs and symptoms (EPS). Other important considerations in the differential diagnosis include central anticholinergic toxicity, heat stroke, drug fever and primary central nervous system (CNS) pathology.
The management of NMS should include 1) immediate discontinuation of antipsychotic drugs and other drugs not essential to concurrent therapy, 2) intensive symptomatic treatment and medical monitoring, and treatment of any concomitant serious medical problems for which specific treatments are available. There is no general agreement about specific pharmacological treatment regimens for uncomplicated NMS.
If a patient requires antipsychotic drug treatment after recovery from NMS, the potential reintroduction of drug therapy should be carefully considered. The patient should be carefully monitored, since recurrences of NMS have been reported.
Pregnancy
Safe use of thiothixene during pregnancy has not been established. Therefore, this drug should be given to pregnant patients only when, in the judgment of the physician, the expected benefits from the treatment exceed the possible risks to mother and fetus.
Non-teratogenic Effects
Neonates exposed to antipsychotic drugs, during the third trimester of pregnancy are at risk for extrapyramidal and/or withdrawal symptoms following delivery. There have been reports of agitation, hypertonia, hypotonia, tremor, somnolence, respiratory distress and feeding disorder in these neonates. These complications have varied in severity; while in some cases symptoms have been self-limited, in other cases neonates have required intensive care unit support and prolonged hospitalization.
Thiothixene Capsules should be used during pregnancy only if the potential benefit justifies the potential risk to the fetus.
Animal reproduction studies and clinical experience to date have not demonstrated any teratogenic effects.
In the animal reproduction studies with thiothixene, there was some decrease in conception rate and litter size, and an increase in resorption rate in rats and rabbits. Similar findings have been reported with other psychotropic agents. After repeated oral administration of thiothixene to rats (5 to 15 mg/kg/day), rabbits (3 to 50 mg/kg/day), and monkeys (1 to 3 mg/kg/day) before and during gestation, no teratogenic effects were seen.
Usage in Children
The use of thiothixene in children under 12 years of age is not recommended because safe conditions for its use have not been established.
As is true with many CNS drugs, thiothixene may impair the mental and/or physical abilities required for the performance of potentially hazardous tasks such as driving a car or operating machinery, especially during the first few days of therapy. Therefore, the patient should be cautioned accordingly.
As in the case of other CNS-acting drugs, patients receiving thiothixene should be cautioned about the possible additive effects (which may include hypotension) with CNS depressants and with alcohol.

PRECAUTIONS

GENERAL PRECAUTIONS

An antiemetic effect was observed in animal studies with thiothixene; since this effect may also occur in man, it is possible that thiothixene may mask signs of over-dosage of toxic drugs and may obscure conditions such as intestinal obstruction and brain tumor.
In consideration of the known capability of thiothixene and certain other psychotropic drugs to precipitate convulsions, extreme caution should be used in patients with a history of convulsive disorders or those in a state of alcohol withdrawal, since it may lower the convulsive threshold. Although thiothixene potentiates the actions of the barbiturates, the dosage of the anticonvulsant therapy should not be reduced when thiothixene is administered concurrently.
Though exhibiting rather weak anticholinergic properties, thiothixene should be used with caution in patients who might be exposed to extreme heat or who are receiving atropine or related drugs. Use with caution in patients with cardiovascular disease.
Caution as well as careful adjustment of the dosages is indicated when thiothixene is used in conjunction with other CNS depressants.

Also, careful observation should be made for pigmentary retinopathy and lenticular pigmentation (fine lenticular pigmentation has been noted in a small number of patients treated with thiothixene for prolonged periods). Blood dyscrasias (agranulocytosis, pancytopenia, thrombocytopenic purpura), and liver damage (jaundice, biliary stasis), have been reported with related drugs.

Antipsychotic drugs, including thiothixene^3, elevate prolactin levels; the elevation persists during chronic administration. Tissue culture experiments indicate that approximately one-third of human breast cancers are prolactin dependent in vitro, a factor of potential importance if the prescription of these drugs is contemplated in a patient with a previously detected breast cancer. Although disturbances such as galactorrhea, amenorrhea, gynecomastia, and impotence have been reported, the clinical significance of elevated serum prolactin levels is unknown for most patients. An increase in mammary neoplasms has been found in rodents after chronic administration of antipsychotic drugs. Published epidemiologic studies have shown inconsistent results when exploring the association between hyperprolactinemia and breast cancer.
Leukopenia, Neutropenia and Agranulocytosis
Class Effect
In clinical trial and/or post-marketing experience, events of leukopenia/neutropenia and agranulocytosis have been reported temporally related to antipsychotic agents.
Possible risk factors for leukopenia/neutropenia include preexisting low white blood cell count (WBC) and history of drug induced leukopenia/neutropenia. Patients with a history of a clinically significant low WBC or drug induced leukopenia/neutropenia should have their complete blood count (CBC) monitored frequently during the first few months of therapy and discontinuation of thiothixene should be considered at the first sign of a clinically significant decline in WBC in the absence of other causative factors.
Patients with clinically significant neutropenia should be carefully monitored for fever or other symptoms or signs of infection and treated promptly if such symptoms or signs occur. Patients with severe neutropenia (absolute neutrophil count < 1000/mm^3) should discontinue thiothixene and have their WBC followed until recovery.

INFORMATION FOR PATIENTS

Given the likelihood that some patients exposed chronically to antipsychotics will develop tardive dyskinesia, it is advised that all patients in whom chronic use is contemplated be given, if possible, full information about this risk. The decision to inform patients and/or their guardians must obviously take into account the clinical circumstances and the competency of the patient to understand the information provided.

DRUG INTERACTIONS

Hepatic microsomal enzyme inducing agents, such as carbamazepine, were found to significantly increase the clearance of thiothixene. Patients receiving these drugs should be observed for signs of reduced thiothixene effectiveness^4,5.
Due to a possible additive effect with hypotensive agents, patients receiving these drugs should be observed closely for signs of excessive hypotension when thiothixene is added to their drug regimen^6.

ADVERSE REACTIONS

NOTE: Not all of the following adverse reactions have been reported with thiothixene. However, since thiothixene has certain chemical and pharmacologic similarities to the phenothiazines, all of the known side effects and toxicity associated with phenothiazine therapy should be borne in mind when thiothixene is used.
Cardiovascular Effects
Tachycardia, hypotension, light-headedness, and syncope. In the event hypotension occurs, epinephrine should not be used as a pressor agent since a paradoxical further lowering of blood pressure may result. Nonspecific EKG changes have been observed in some patients receiving thiothixene. These changes are usually reversible and frequently disappear on continued thiothixene therapy. The incidence of these changes is lower than that observed with some phenothiazines. The clinical significance of these changes is not known.
CNS Effects
Drowsiness, usually mild, may occur although it usually subsides with continuation of thiothixene therapy. The incidence of sedation appears similar to that of the piperazine group of phenothiazines but less than that of certain aliphatic phenothiazines. Restlessness, agitation and insomnia have been noted with thiothixene. Seizures and paradoxical exacerbation of psychotic symptoms have occurred with thiothixene infrequently.
Hyperreflexia has been reported in infants delivered from mothers having received structurally related drugs.
In addition, phenothiazine derivatives have been associated with cerebral edema and cerebrospinal fluid abnormalities.
Extrapyramidal Symptoms
Extrapyramidal symptoms, such as pseudoparkinsonism, akathisia and dystonia have been reported (see Adverse Reactions: Dystonia: Class Effect). Management of these extrapyramidal symptoms depends upon the type and severity. Rapid relief of acute symptoms may require the use of an injectable antiparkinson agent. More slowly emerging symptoms may be managed by reducing the dosage of thiothixene and/or administering an oral antiparkinson agent.
Dystonia
Class Effect
Symptoms of dystonia, prolonged abnormal contractions of muscle groups, may occur in susceptible individuals during the first few days of treatment. Dystonic symptoms include: spasm of the neck muscles, sometimes progressing to tightness of the throat, swallowing difficulty, difficulty breathing, and/or protrusion of the tongue. While these symptoms can occur at low doses, they occur more frequently and with greater severity with high potency and at higher doses of first generation antipsychotic drugs. An elevated risk of acute dystonia is observed in males and younger age groups.
Persistent Tardive Dyskinesia
As with all antipsychotic agents, tardive dyskinesia may appear in some patients on long-term therapy with thiothixene, or may occur after drug therapy has been discontinued. The syndrome is characterized by rhythmical involuntary movements of the tongue, face, mouth or jaw (e.g., protrusion of tongue, puffing of cheeks, puckering of mouth, chewing movements). Sometimes these may be accompanied by involuntary movements of extremities.
Since early detection of tardive dyskinesia is important, patients should be monitored on an ongoing basis. It has been reported that fine vermicular movement of the tongue may be an early sign of the syndrome. If this or any other presentation of the syndrome is observed, the clinician should consider possible discontinuation of antipsychotic medication. (See WARNINGS.)
Hepatic Effects
Elevations of serum transaminase and alkaline phosphatase, usually transient, have been infrequently observed in some patients. No clinically confirmed cases of jaundice attributable to thiothixene have been reported.
Hematologic Effects
As is true with certain other psychotropic drugs, leukopenia and leucocytosis, which are usually transient, can occur occasionally with thiothixene. Other antipsychotic drugs have been associated with agranulocytosis, eosinophilia, hemolytic anemia, thrombocytopenia and pancytopenia.
Allergic Reactions
Rash, pruritus, urticaria, photosensitivity and rare cases of anaphylaxis have been reported with thiothixene. Undue exposure to sunlight should be avoided. Although not experienced with thiothixene, exfoliative dermatitis and contact dermatitis (in nursing personnel) have been reported with certain phenothiazines.
Endocrine/Reproductive
Hyperprolactinemia^3, lactation, menstrual irregularities, moderate breast enlargement and amenorrhea have occurred in a small percentage of females receiving thiothixene. If persistent, this may necessitate a reduction in dosage or the discontinuation of therapy. Phenothiazines have been associated with false positive pregnancy tests, gynecomastia, hypoglycemia, hyperglycemia and glycosuria.
Autonomic Effects
Dry mouth, blurred vision, nasal congestion, constipation, increased sweating, increased salivation and impotence have occurred infrequently with thiothixene therapy. Phenothiazines have been associated with miosis, mydriasis, and adynamic ileus.
Other Adverse Reactions
Hyperpyrexia, anorexia, nausea, vomiting, diarrhea, increase in appetite and weight, weakness or fatigue, polydipsia, and peripheral edema.
Although not reported with thiothixene, evidence indicates there is a relationship between phenothiazine therapy and the occurrence of a systemic lupus erythematosus-like syndrome.
Neuroleptic Malignant Syndrome (NMS)
Please refer to the text regarding NMS in the WARNINGS section.
NOTE: Sudden deaths have occasionally been reported in patients who have received certain phenothiazine derivatives. In some cases, the cause of death was apparently cardiac arrest or asphyxia due to failure of the cough reflex. In others, the cause could not be determined nor could it be established that death was due to phenothiazine administration.

DOSAGE & ADMINISTRATION

Dosage of thiothixene capsules should be individually adjusted depending on the chronicity and severity of the symptoms of schizophrenia. In general, small doses should be used initially and gradually increased to the optimal effective level, based on patient response.
Some patients have been successfully maintained on once a day thiothixene capsule therapy.
The use of thiothixene capsules in children under 12 years of age is not recommended because safe conditions for its use have not been established.
In milder conditions, an initial dose of 2 mg three times daily is recommended. If indicated, a subsequent increase to 15 mg/day total daily dose is often effective.
In more severe conditions, an initial dose of 5 mg twice daily is recommended.
The usual optimal dose is 20 mg to 30 mg daily. If indicated, an increase to 60 mg/day total daily dose is often effective. Exceeding a total daily dose of 60 mg rarely increases the beneficial response.

OVERDOSAGE

Manifestations include muscular twitching, drowsiness and dizziness. Symptoms of gross overdosage may include CNS depression, rigidity, weakness, torticollis, tremor, salivation, dysphagia, hypotension, disturbances of gait, or coma.
Treatment
Essentially symptomatic and supportive. Early gastric lavage is helpful. Keep patient under careful observation and maintain an open airway, since involvement of the extrapyramidal system may produce dysphagia and respiratory difficulty in severe overdosage. If hypotension occurs, the standard measures for managing circulatory shock should be used (I.V. fluids and/or vasoconstrictors).
If a vasoconstrictor is needed, norepinephrine and phenylephrine are the most suitable drugs. Other pressor agents, including epinephrine, are not recommended, since phenothiazine derivatives may reverse the usual pressor action of these agents and cause further lowering of blood pressure.
If CNS depression is marked, symptomatic treatment is indicated. Extrapyramidal symptoms may be treated with antiparkinson drugs.
There are no data on the use of peritoneal or hemodialysis, but they are known to be of little value in phenothiazine intoxication.

HOW SUPPLIED

Thiothixene Capsules, USP are available containing 1 mg, 2 mg, 5 mg or 10 mg of thiothixene, USP.

Thiothixene, USP 1 mg capsule is a size 4 hard gelatin capsule with a caramel opaque cap and a blue opaque body filled with white to off-white powder. The capsule is imprinted “014” on the cap and “novitium” on the body in black ink. They are available as below:

NDC 51407-275-01 Bottle of 100 capsules

Thiothixene, USP 2 mg capsule is a size 4 hard gelatin capsule with a caramel opaque cap and a yellow opaque body filled with white to off-white powder. The capsule is imprinted “015” on the cap and “novitium” on the body in black ink. They are available as below:

NDC 51407-276-01 Bottle of 100 capsules

Thiothixene, USP 5 mg capsule is a size 4 hard gelatin capsule with a caramel opaque cap and a white opaque body filled with white to off-white powder. The capsule is imprinted “016” on the cap and “novitium” on the body in black ink. They are available as below:

NDC 51407-277-01 Bottle of 100 capsules

Thiothixene, USP 10 mg capsule is a size 4 hard gelatin capsule with a caramel opaque cap and a peach opaque body filled with white to off-white powder. The capsule is imprinted “017” on the cap and “novitium” on the body in black ink. They are available as below:

NDC 51407-278-01 Bottle of 100 capsules

Store at 20° to 25°C (68° to 77°F). [See USP Controlled Room Temperature.] Protect from light.

Preserve in tight, light-resistant container as defined in the USP.

REFERENCES

1. Worldwide Labeling Safety Report: Dyskinesia and Dyskinesia Tardive and Thiothixene, (16Apr02).
2. Worldwide Labeling Safety Report: Neuroleptic Malignant Syndrome and Thiothixene, (16Apr02).
3. Worldwide Labeling Safety Report: Hyperprolactinemia and Thiothixene, (16Apr02).
4. Ereshefsky L, Saklad SR, Watanabe MD, et al. Thiothixene Pharmacokinetic Interactions: A Study of Hepatic Enzyme Inducers, Clearance Inhibitors, and Demographic Variables. Journal of Clinical Psychopharmacology,11(5):296–301, (1991).
5. Worldwide Labeling Safety Report: Drug Interaction and Thiothixene, (09May02).
6. McEvoy GK, Miller JL, Snow EK, et al. AHFS Drug Information. American Society of Health- System Pharmacists, Inc., p. 2334-2336, (2002).
7. Worldwide Labeling Safety Report: Menstrual Disorder and Thiothixene, (16Apr02).

Manufactured by:

Novitium Pharma LLC

70 Lake Drive, East Windsor

New Jersey 08520

Issued: 02/2025

LB4118-04

Marketed by:

GSMS, Inc.

Camarillo, CA 93012 USA

PACKAGE LABEL.PRINCIPAL DISPLAY PANEL

Thiothixene Capsules, USP 1 mg 100's counts
Thiothixene Capsules, USP 2 mg 100's counts
Thiothixene Capsules, USP 5 mg 100's counts
Thiothixene Capsules, USP 10 mg 100's counts